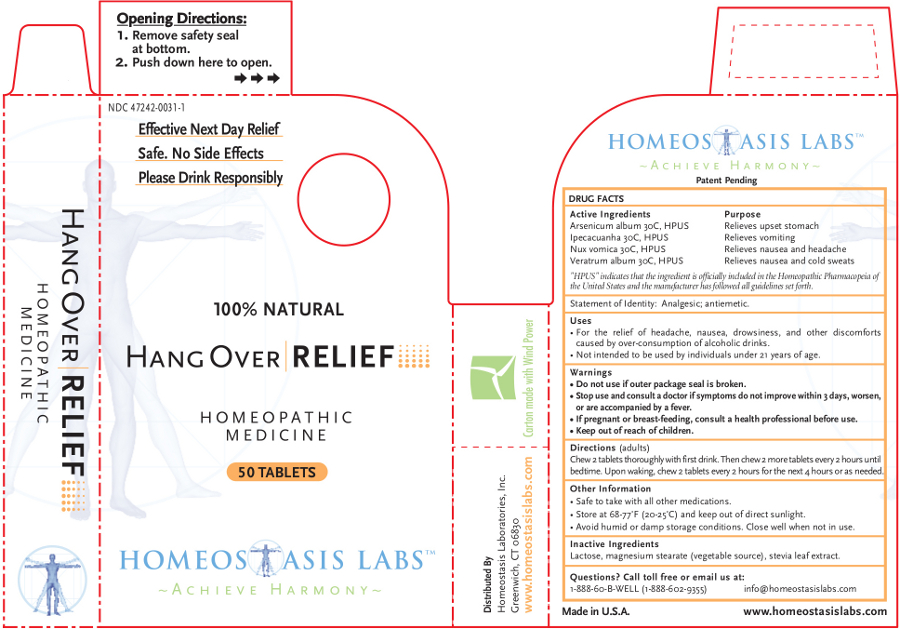 DRUG LABEL: Hang Over RELIEF
NDC: 47242-0031 | Form: TABLET, CHEWABLE
Manufacturer: Homeostasis Laboratories, Inc.
Category: homeopathic | Type: HUMAN OTC DRUG LABEL
Date: 20121114

ACTIVE INGREDIENTS: ARSENIC TRIOXIDE 30 [hp_C]/1 1; IPECAC 30 [hp_C]/1 1; STRYCHNOS NUX-VOMICA SEED 30 [hp_C]/1 1; VERATRUM ALBUM ROOT 30 [hp_C]/1 1
INACTIVE INGREDIENTS: LACTOSE; MAGNESIUM STEARATE; STEVIA REBAUDIUNA LEAF

Hang Over RELIEF

Active Ingredients | Purpose
Arsenicum album 30C, HPUS | Relieves upset stomach
Ipecacuanha 30C, HPUS | Relieves vomiting
Nux vomica 30C, HPUS | Relieves nausea and headache
Veratrum album 30C, HPUS | Relieves nausea and cold sweats

"HPUS" indicates that the ingredient is officially included in the Homeopathic Pharmacopeia of the United States and the manufacturer has followed all guidelines set forth.

Statement of Identity: Analgesic; antiemetic.

Uses

For the relief of headache, nausea, drowsiness, and other discomforts caused by over-consumption of alcoholic drinks.

Not intended to be used by individuals under 21 years of age.

Warnings

- Do not use if outer package seal is broken.
- Stop use and consult a doctor if symptoms do not improve within 3 days, worsen, or are accompanied by a fever.

PREGNANCY OR BREAST FEEDING

- If pregnant or breast-feeding, consult a health professional before use.

- Keep out of reach of children.

Directions

(adults)

Chew 2 tablets thoroughly with first drink. Then chew 2 more tablets every 2 hours until bedtime. Upon waking, chew two tablets every 2 hours for the next four hours or as needed.

Other information

- Safe to take with all other medications.
- Store at 68-77°F (20-25°C) and keep out of direct sunlight.
- Avoid humid or damp storage conditions. Close well when not in use.

Inactive Ingredients

Lactose, magnesium stearate (vegetable source), stevia leaf extract.

Questions? Call toll free or email us at:

1-888-60-B-WELL (1-888-602-9355)

info@homeostasislabs.com